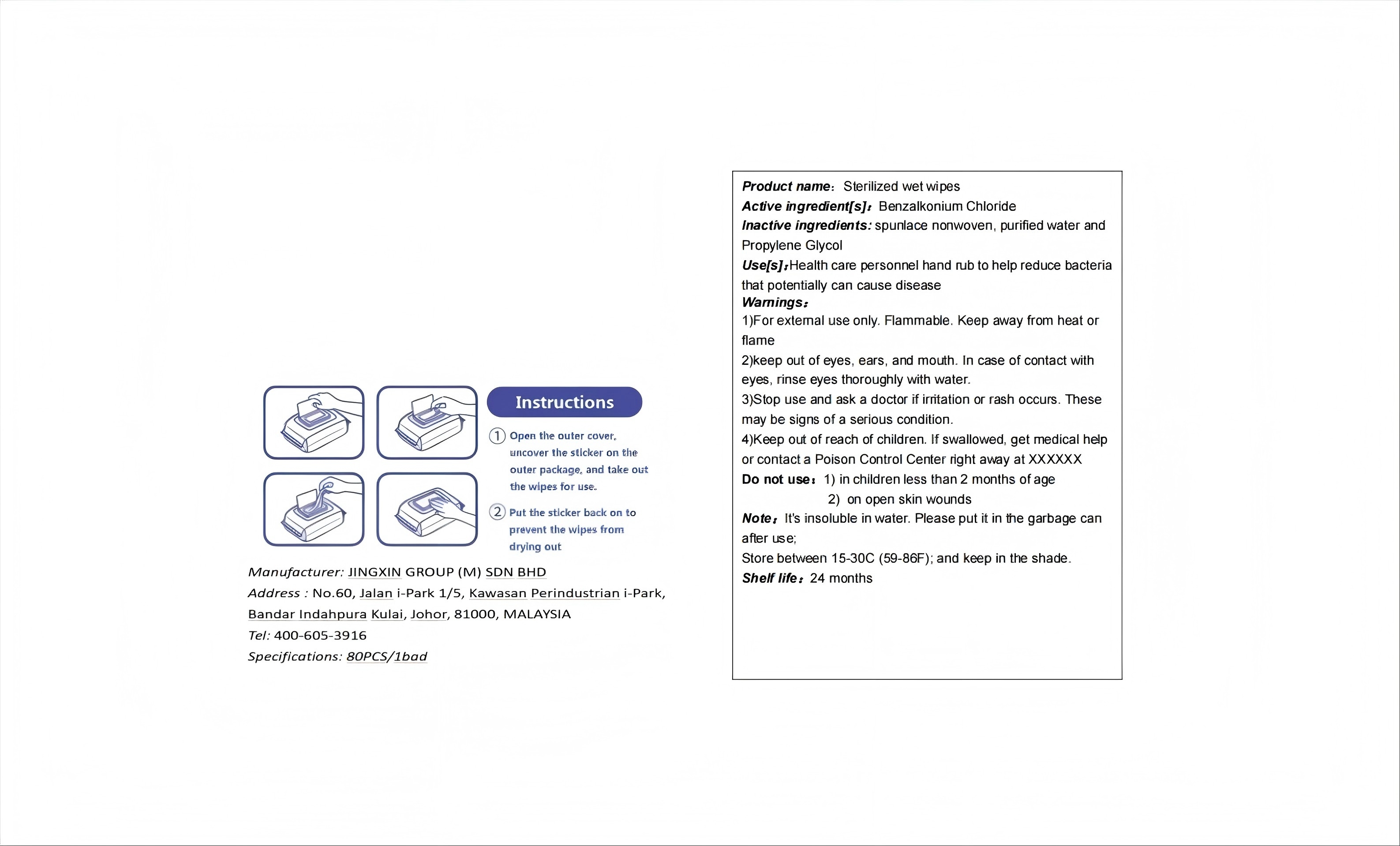 DRUG LABEL: Sterilized wet wipes
NDC: 85868-001 | Form: DRESSING
Manufacturer: JINGXIN GROUP (M) SDN BHD
Category: otc | Type: HUMAN OTC DRUG LABEL
Date: 20250707

ACTIVE INGREDIENTS: BENZETHONIUM CHLORIDE 0.0018 g/1 g
INACTIVE INGREDIENTS: WATER 0.9967 g/1 g; PROPYLENE GLYCOL 0.0015 g/1 g

ACTIVE INGREDIENT

BENZALKONIUM CHLORIDE

PURPOSE

Antiseptic, Hand Sanitizer

INDICATIONS AND USAGE

Hand Sanitizer to help reduce bacteria that potentially can cause disease. For use when soap and water are not available.

WARNINGS

For external use only. Flammable. Keep away from heat or flame.

DO NOT USE

in children less than 2 months of age.

on open shin wounds.

When using this product keep out of eyes, ears, and mouth. In case of contact with eyes, rinse eyes thouroughly with water.

STOP USE

Stip use and ack a doctor if irritation or rash occurs. These may be signs of a serious condition.

Keep out of reach of children. If swallowed, get medical help or contact a Poison Control Center right away.

DOSAGE AND ADMINISTRATION

Place enough product on hands to cover all surfaces.

STORAGE AND HANDLING

Store between 15-30C (59-86F).

Avoid freezing and excessive heat above 40C (104F).

INACTIVE INGREDIENT

CELLULOSE, WATER, CETYLPYRIDINIUM CHLORIDE, BENZETHONIUM CHLORIDE, PROPYLENE GLYCOL